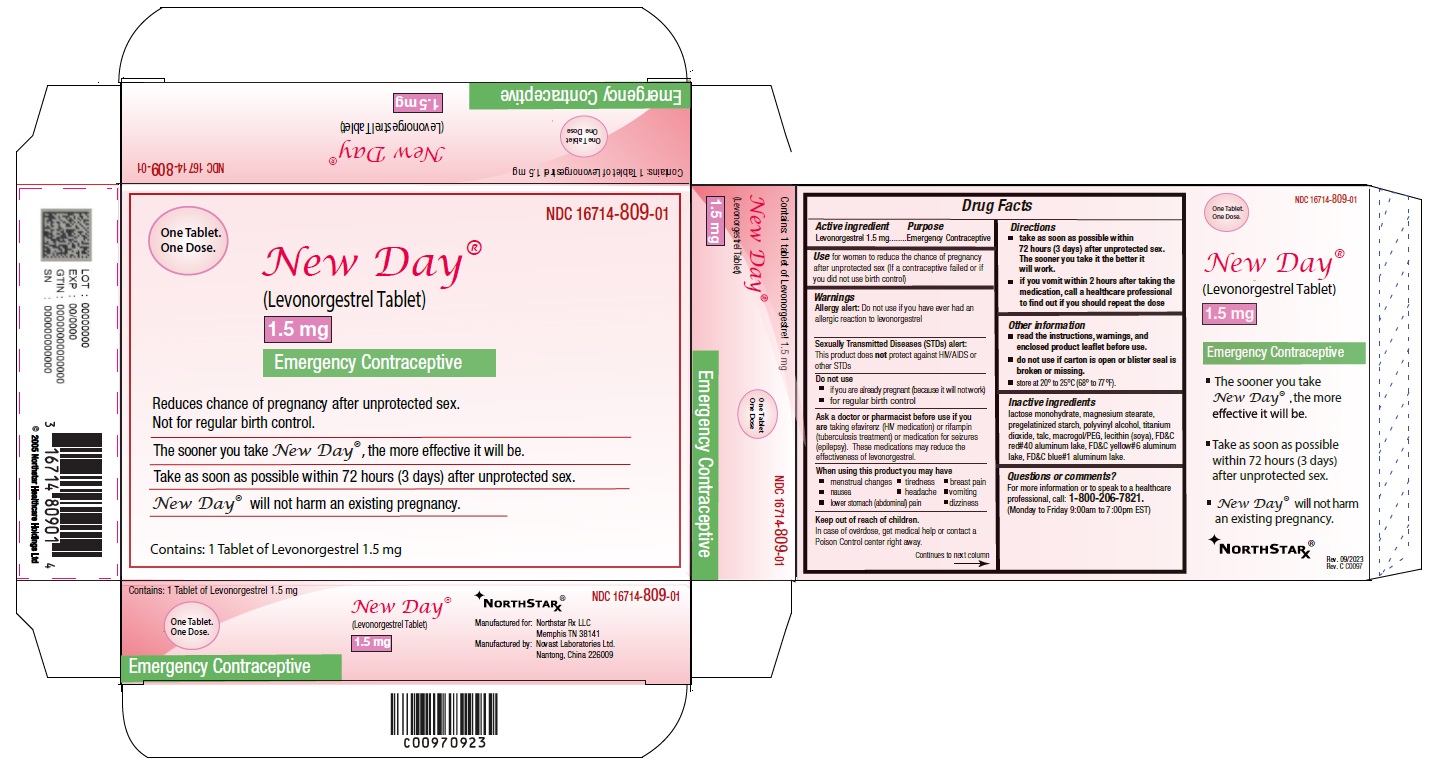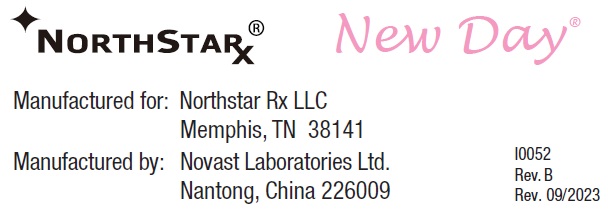 DRUG LABEL: New Day
NDC: 16714-809 | Form: TABLET
Manufacturer: Northstar Rx LLC
Category: otc | Type: HUMAN OTC DRUG LABEL
Date: 20251205

ACTIVE INGREDIENTS: LEVONORGESTREL 1.5 mg/1 1
INACTIVE INGREDIENTS: MAGNESIUM STEARATE; LACTOSE MONOHYDRATE; STARCH, PREGELATINIZED CORN; POLYVINYL ALCOHOL; TITANIUM DIOXIDE; TALC; POLYETHYLENE GLYCOL 3350; LECITHIN, SOYBEAN; FD&C RED NO. 40; FD&C YELLOW NO. 6; FD&C BLUE NO. 1

New Day® (Levonorgestrel Tablet, 1.5mg)

Active Ingredient

Levonorgestrel 1.5mg

Purpose

Emergency Contraceptive

Use

Use for women to reduce the chance of pregnancy after unprotected sex (if a contraceptive failed or if you did not use birth control)

Warnings

Allergy alert: Do not use if you have ever had an allergic reaction to levonorgestrel

Sexually Transmitted Diseases (STDs) alert: This product does not protect against HIV/AIDS or other STDs

Do not use

•if you are already pregnant (because it will not work)

•for regular birth control

Ask a doctor or pharmacist before use if you are

taking efavirenz (HIV medication) or rifampin (tuberculosis treatment) or medication for seizures (epilepsy). These medications may reduce the effectiveness of levonorgestrel.

When using this product you may have

• menstrual changes

• nausea

• lower stomach (abdominal) pain

• tiredness

• headache

• dizziness

• breast pain

• vomiting

Keep out of reach of children.

In case of overdose, get medical help or contact a Poison Control center right away.

DIRECTIONS

•take as soon as possible within 72 hours (3 days) after unprotected sex. The sooner you take it the better it will work.

•if you vomit within 2 hours after taking the medication, call a healthcare professional to find out if you should repeat the dose

Other information

•read the instructions, warnings, and enclosed product leaflet before use.

•do not use if carton is open or blister seal is broken or missing.

•store at 20° to 25°C (68° to 77°F).

Inactive ingredients

lactose monohydrate, magnesium stearate, pregelatinized starch, polyvinyl alcohol, titanium dioxide, talc, macrogol/PEG, lecithin (soya), FD&C red#40 aluminum lake, FD&C yellow#6 aluminum lake, FD&C blue#1 aluminum lake.

Questions or comments?

For more information or to speak to a healthcare professional, call: 1-800-206-7821.(Monday to Friday 9:00am to 7:00pm EST)

New Day

(Levonorgestrel Tablet) 1.5 mg

emergency contraceptive

One Tablet. One Dose.

What you need to know

1 Blister Card with 1 Tablet.

What is New Day®?

New Day® is emergency contraception that helps prevent pregnancy after birth control failure or unprotected sex. It is a backup method of preventing pregnancy and should not be used as regular birth control.

What New Day® is not.

New Day® will not work if you are already pregnant and will not affect an existing pregnancy. New Day® will not protect you from HIV infection (the virus that causes AIDS) and other sexually transmitted diseases (STDs).

When should I use New Day®?

The sooner you take emergency contraception, the better it works. You should use New Day® within 72 hours (3 days) after you have had unprotected sex.

New Day® is a backup or emergency method of birth control you can use when:

•your regular birth control was used incorrectly or failed

•you did not use any birth control method

When not to use New Day®.

New Day® should not be used:

•as a regular birth control method, because it's not as effective as regular birth control.

•if you are already pregnant, because it will not work.

•if you are allergic to levonorgestrel or any other ingredients in New Day®.

When should I talk to a doctor or pharmacist?

Ask a doctor or pharmacist before use if you are taking efavirenz (HIV medication) or rifampin (tuberculosis treatment) or medication for seizures (epilepsy). These medications may reduce the effectiveness of New Day®and increase your chance of becoming pregnant. Your doctor may prescribe another form of emergency contraception that may not be affected by these medications.

How does New Day® work?

New Day® works before release of an egg from the ovary. As a result, New Day® usually stops or delays the release of an egg from the ovary. New Day® is one tablet that contains a higher dose of levonorgestrel than birth control pills and works in a similar way to prevent pregnancy.

How can I get the best results from New Day®?

You have 72 hours (3 days) to try to prevent pregnancy after birth control failure or unprotected sex. The sooner you take New Day®, the better it works.

How effective is New Day®?

If New Day® is taken as directed, it can significantly decrease the chance that you will get pregnant. About 7 out of every 8 women who would have gotten pregnant will not become pregnant.

How will I know New Day® worked?

You will know New Day® has been effective when you get your next period, which should come at the expected time, or within a week of the expected time. If your period is delayed beyond 1 week, it is possible you may be pregnant. You should get a pregnancy test and follow up with your healthcare professional.

Will I experience any side effects?

•some women may have changes in their period, such as a period that is heavier or lighter or a period that is early or late. If your period is more than a week late, you may be pregnant.

•if you have severe abdominal pain, you may have an ectopic pregnancy, and should get immediate medical attention.

•when used as directed, New Day® is safe and effective. Side effects may include changes in your period, nausea, lower stomach (abdominal) pain, tiredness, headache, dizziness, and breast tenderness.

•if you vomit within 2 hours of taking the medication, call a healthcare professional to find out if you should repeat the dose.

What if I still have questions about New Day®?

If you have questions or need more information, call our toll-free number, 1-800-206-7821.

Other Information

Keep out of reach of children:

In case of overdose, get medical help or contact a Poison Control Center right away at 1-800-222-1222.

Do not use if the blister seal is opened.

Store at room temperature 20° to 25°C (68° to 77°F).

Active ingredient: levonorgestrel 1.5 mg

Inactive ingredients: magnesium stearate, lactose monohydrate, pregelatinized starch, polyvinyl alcohol, titanium dioxide, talc, macrogol/PEG, lecithin (soya), FD&C red#40 aluminum lake, FD&C yellow#6 aluminum lake, FD&C blue#1 aluminum lake.

If you are sexually active, you should see a healthcare provider for routine checkups. Your healthcare provider will talk to you about and, if necessary, test you for sexually transmitted diseases, teach you about effective methods of routine birth control, and answer any other questions you may have.